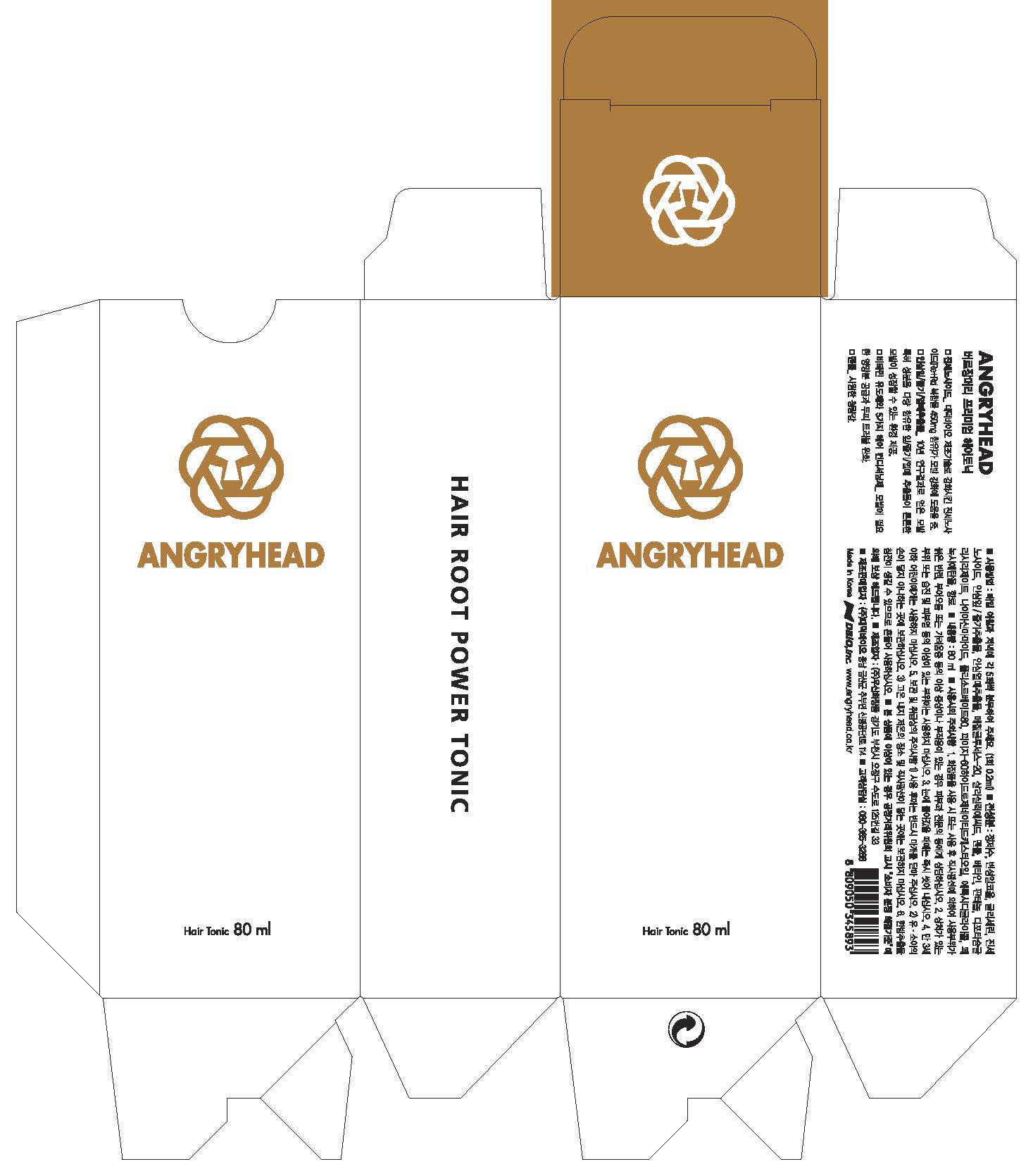 DRUG LABEL: Angryhead Premium Hair Tonic
NDC: 58906-0004 | Form: LIQUID
Manufacturer: DBIO Inc
Category: otc | Type: HUMAN OTC DRUG LABEL
Date: 20171009

ACTIVE INGREDIENTS: SALICYLIC ACID 0.1 g/100 mL
INACTIVE INGREDIENTS: WATER; BUTYLENE GLYCOL

Drug Facts

ACTIVE INGREDIENT

salicylic acid

INACTIVE INGREDIENT

Cocamidopropyl Betaine, Sodium Lauroyl Methylaminopropionate, TEA-Cocoyl Glutamate, Disodium Laureth Sulfosuccinate, Chamaecyparis Obtusa Water, Cocamide MEA, PEG-150 Disterate, Polyquaternium-10, PPG-3 Myristyl Ether, Sodium Benzoate, Water, Ginkgo Bilboa Leaf Extract, Butylene Glycol, Phenoxyethanol, Panthenol, Pentasodum Pentetate, Tromethamine, Trehalose, Butylene Glycol, Panax Ginseng Root Extract, Thuja Occidentalis Leaf Extract, Morus Alba Bark Extract, Chrysanthemum Zawadskii Extract, Lycium Chinese Fruit Extract, Acorus Gramineus Root/Stem Extract, Xanthium Strumarium Fruit Extract, Glycyrrhiza Glabra(Licorice) Root Extract, Mentha Arvensis Extract, Phenoxyethanol, PCA, Sodium Chloride, Niacinamide, Panax Ginseng Root Extract, Guar Hydroxypropyltrimonium Chloride

PURPOSE

Prevents hair loss, thickens hair root and enables improvement on your scalp.

keep out of reach of the children

INDICATIONS AND USAGE

1. Wet your hair with warm water.
2. Apply small amount of toner on the scalp area.
- If contact with eyes occurs, rinse immediately with water

WARNINGS

Cautions :

1. When you use this product and find any of following problems, stop using it. if you keep using it despite the problem, the symptom will get worse, so you will have to go see a dermatologist.

- During use, if you have red spots, swelling, itching, or any other stimuli.

- if the applied region has any problem above for direct light.

2. Do not use the product on wound or dermatitis. 3.Attentive points for storage and treatment :

- Store it in the place where infants or children cannot touch

- do not store it where it has either high or low temperature or there is direct light.

DOSAGE AND ADMINISTRATION

for external use only